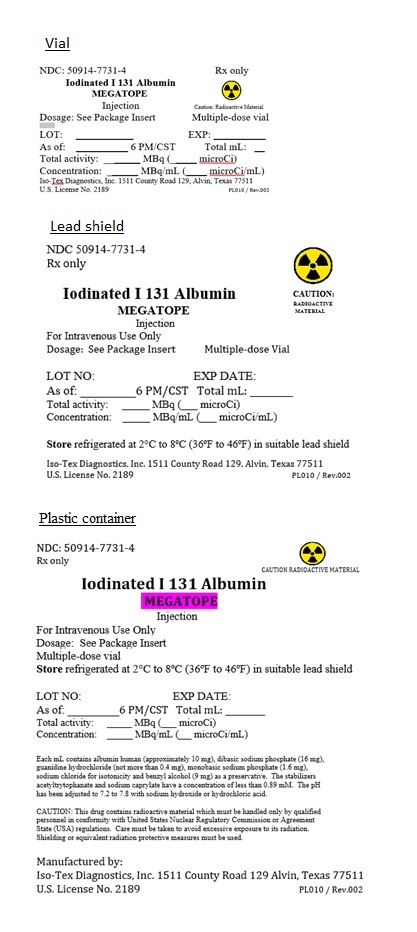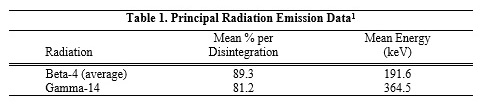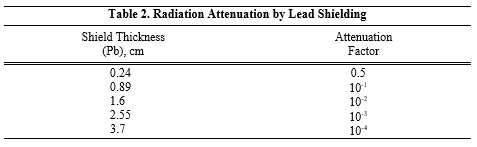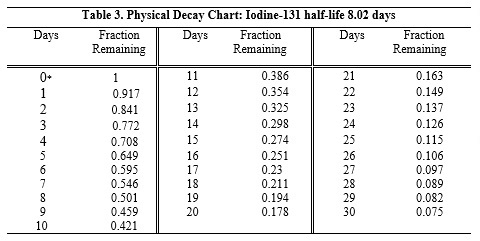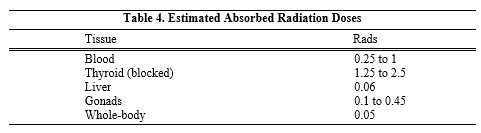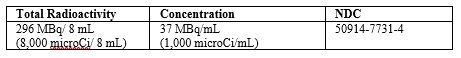 DRUG LABEL: Megatope
NDC: 50914-7731 | Form: INJECTION, SOLUTION
Manufacturer: Iso-Tex Diagnostics, Inc.
Category: prescription | Type: HUMAN PRESCRIPTION DRUG LABEL
Date: 20230901

ACTIVE INGREDIENTS: HUMAN SERUM ALBUMIN I-131 1 mCi/1 mL
INACTIVE INGREDIENTS: ALBUMIN HUMAN; BENZYL ALCOHOL

MEGATOPE

Rx only.

DESCRIPTION

Chemical Characteristics
MEGATOPE (iodinated I 131 albumin) injection is a sterile, nonpyrogenic, radioactive diagnostic agent for intravenous use. Each mL contains albumin human (approximately 10 mg), dibasic sodium phosphate (16 mg), guanidine hydrochloride (not more than 0.4 mg), monobasic sodium phosphate (1.6 mg), sodium chloride for isotonicity, and benzyl alcohol (9 mg) as a preservative. The stabilizers acetyltryptophanate and sodium caprylate have a concentration of less than 0.89 mM. The pH has been adjusted to 7.2 to 7.8 with sodium hydroxide or hydrochloric acid. Each vial contains 37 MBq/mL (1,000 microCi/mL) of radioactivity as iodinated I 131 albumin at time of calibration (see HOW SUPPLIED).

Physical Characteristics Iodine-131 decays by beta and gamma emissions with a physical half-life of 8.02 days. Photons that are useful for detection and imaging studies are listed in Table 1.

^1 Evaluated Nuclear Structure Data File of the Oak Ridge Nuclear Data Project DOE (1985).

External Radiation
The specific gamma ray constant for iodine-131 is 2.2 R/hour-millicurie at 1 cm. The first half-value layer is 0.24 cm lead (Pb). A range of values for the relative attenuation of the radiation emitted by this radionuclide that result from interposition of various thicknesses of Pb is shown in Table 2. To facilitate control of the radiation exposure from this radionuclide, the use of a 2.55 cm thickness of Pb will attenuate the radiation emitted by a factor of about 1,000.

To correct for physical decay of iodine-131, the fractions that remain at selected intervals after the time of calibration are shown in Table 3.

* Calibration time

CLINICAL PHARMACOLOGY

Following intravenous injection, iodinated I 131 albumin is distributed throughout the intravascular pool within 10 minutes; extravascular distribution takes place more slowly. Iodinated I 131 albumin also can be detected in the lymph and in certain body tissues within 10 minutes after injection, but maximum distribution of radioactivity throughout the extravascular space does not occur until two to four days after administration. The time at which extravascular activity is maximal has been designated as the “equilibrium time.” When this point has been reached, the radioactivity remaining in the intravascular and extravascular spaces decreases slowly and exponentially in parallel fashion.

The administered radioactivity is eliminated almost entirely in the urine, only about 2 percent of the total dose ultimately appears in the feces.

The biologic half-life of iodinated I 131 albumin is dependent upon a number of factors, and published studies have varied considerably in their reporting of this figure. It has ranged, in the literature, from below 10 days to over 20 days. One important factor affecting the biologic half-life is the initial rate of excretion, and this depends in part on the quality of the iodinated I 131 albumin. With MEGATOPE, the biologic half-life in normal individuals has been reported to be approximately 14 days.

INDICATIONS AND USAGE

MEGATOPE is indicated in adults for use in determinations of total blood and plasma volumes.

CONTRAINDICATIONS

None Known.

WARNINGS

Aseptic meningitis and pyrogenic reactions have been reported following cisternography with MEGATOPE. The safety and effectiveness of MEGATOPE for cisternography have not been established. MEGATOPE is not approved for this use.

PRECAUTIONS

General
In the use of any radioactive material, care should be taken to minimize radiation exposure to the patient and healthcare providers consistent with proper patient management.

Radiopharmaceuticals should be used by or under control of healthcare providers who are qualified by specific training and experience in the safe use and handling of radionuclides and whose experience and training have been approved by the appropriate government agency authorized to license the use of radionuclides.

Carcinogenesis, Mutagenesis, Impairment of Fertility
No long-term animal studies have been performed to evaluate carcinogenic potential or whether iodinated I 131 albumin affects fertility in males or females.

Pregnancy
Iodine-131 crosses the placenta and can permanently impair fetal thyroid function. MEGATOPE should be administered to a pregnant woman only if clearly needed. Administration of an appropriate thyroid blocking agent is recommended before use of MEGATOPE in a pregnant woman to protect the woman and fetus from accumulation of iodine-131 (see DOSAGE AND ADMINISTRATION).

There are no data on iodinated I 131 albumin use in pregnant women to evaluate for a drug-associated risk of major birth defects, miscarriage or other adverse maternal or fetal outcomes. Animal reproduction studies have not been conducted. All radiopharmaceuticals have the potential to cause fetal harm depending on the fetal stage of development and the magnitude of the radiation dose.

The estimated background risk of major birth defects and miscarriage for the indicated population is unknown. All pregnancies have a background risk of birth defect, loss, or other adverse outcomes. In the U.S. general population, the estimated background risk of major birth defects and miscarriage in clinically recognized pregnancies is 2 - 4% and 15 - 20%, respectively.

Nursing Mothers
Iodine-131 is present in human milk. There are no data on the effect of iodinated I 131 albumin on the breastfed infant or milk production. Because of the potential for serious adverse reactions in the breastfed infant, including transient hypothyroidism, advise women not to breastfeed during treatment with MEGATOPE and for 80 days after the final dose.

Pediatric Use
Safety and effectiveness of MEGATOPE in pediatric patients have not been established.

Geriatric Use
Clinical studies of MEGATOPE did not include sufficient numbers of subjects aged 65 and over to determine whether they respond differently from younger subjects. Other reported clinical experience has not identified differences in responses between the elderly and younger patients.

ADVERSE REACTIONS

The following adverse reactions have been identified with the use of radioiodinated albumin products. Because these reactions are reported voluntarily from a population of uncertain size, it is not always possible to reliably estimate their frequency or establish a causal relationship to drug exposure.

Immune System Disorders: Hypersensitivity

DOSAGE AND ADMINISTRATION

Premedication
Administer 10 drops of Strong Iodine Solution, USP (e.g., Lugol’s Solution) three times daily, beginning at least 24 hours before administration of MEGATOPE and continue for 1 week or 2 weeks thereafter to minimize the uptake of iodine-131.

Recommended Dosage
The recommended dose of MEGATOPE for total blood or plasma volume determination in adult patients is from 0.185 MBq to 1.85 MBq (5 microCi to 50 microCi) administered intravenously.

When a procedure such as a blood volume is to be repeated, do not exceed 7.4 MBq (200 microCi) in any 1 week.

Administration Instructions
• Measure the patient dose using a suitable dose calibrator immediately prior to administration.
• Use a shielded syringe for withdrawing and injecting MEGATOPE.
• Parenteral drug products should be inspected visually for particulate matter and discoloration prior to administration whenever solution and container permit. MEGATOPE is a colorless to very pale yellow solution. Do not use MEGATOPE if excessive coloration is present.
• The expiration date given on the MEGATOPE vial label pertains to the stability of MEGATOPE and not to the radioactivity level.

Blood Volume Determination
Preparation of Reference Solution
1. Remove the amount from the vial to be used in the procedure identical in volume to the dose to be administered to the patient.
2. Prepare a reference solution using 0.9% Sodium Chloride Injection, USP as a diluent. The recommended dilution is 1:4,000 [Dilution Factor (DF) = 4,000].
3. Determine the radioactivity concentration (net cpm/mL) of the reference solution.
4. Assay the reference solution and the blood samples (Step 3 of Administration of Dose) using the same geometric configuration.

Administration of Dose
1. Inject the dose into a large vein in patient’s arm. Measure the residual radioactivity in the syringe and needle.
2. Do not reuse the syringe. Dispose the syringe in accordance with the US Nuclear Regulatory Commission or Agreement State regulations pertaining to the disposal of radioactive waste.
3. At 5 minutes and 15 minutes after injecting the dose, withdraw blood samples from the patient’s other arm with a sterile heparinized syringe.

Calculation of Blood Volume
1. Take a known aliquot from each blood sample and determine radioactivity concentration in net cpm/mL.
2. Plot the 5-minute and 15- minute sample counts (net cpm/mL) on semilog graph paper using the average count value of each sample and determine the radioactivity concentration at injection time (zero time) by drawing a straight line through the 15-minute and 5-minute points to zero time. The x ordinate of the graph is the sample withdrawal time and the logarithmic y ordinate is radioactivity concentration in net cpm/mL.
3. Calculate patient’s blood volume (in mL) using the following formula:

Net cpm/mL reference solution x DF* = blood volume (in mL)

Net cpm/mL patient's blood sample

*DF: Dilution factor of reference solution

Sample Blood Volume Calculations
Volume of blood sample aliquot = 1 mL
Volume of reference solution aliquot = 1 mL
Net counts at zero time = 48,100
Net counts obtained from reference solution aliquot = 52,430

Using the formula above gives 52,430 x 4,000 = 4,360 mL
48,100

Serial Blood Volume Determinations
• Use a low dose of MEGATOPE to permit repetitions as often as required by clinical circumstances.
• In each determination after the first dose, correct the background radioactivity remaining in the blood from former determinations by subtracting the radioactivity concentration of a blood sample obtained before the injection of MEGATOPE (i.e., background blood sample) from the radioactivity concentration of a post-injection blood sample.

Background Blood Sample
1. Prior to injecting MEGATOPE, withdraw background blood sample from large vein in patient’s arm with a sterile heparinized syringe.
2. Leaving needle in patient’s vein, detach syringe containing blood sample.
3. Attach syringe containing the dose of MEGATOPE to the indwelling needle and administer (see instructions under Blood Volume Determination, Administration of Dose).
4. Determine radioactivity concentration in net cpm/mL of aliquots taken from background and post-injection blood samples, and from the reference solution.

Calculation of Blood Volume
Subtract the radioactivity concentration (net cpm/mL) per aliquot of the background blood sample from the radioactivity concentration per aliquot of the blood sample obtained after the injection of MEGATOPE. The formula for calculating each blood volume determination after the first one thus becomes:

Net cpm/mL reference solution x DF* = blood volume (in mL)
Net cpm/mL Net cpm/mL
postinjection minus background
blood sample blood sample

*DF: Dilution Factor of reference solution

Plasma Volume Determination
The procedure is essentially the same as that for blood volume determination, except that the blood sample drawn from the patient is centrifuged, the red blood cells are removed, and net cpm /mL of the plasma is determined. The formula for calculation of plasma volume, therefore, is:

Net cpm/mL reference solution x DF* = plasma volume (in mL)
Net cpm/mL patient's plasma sample

*DF: Dilution factor of reference solution

Radiation Dosimetry
The estimated absorbed radiation doses to an adult patient from an intravenous injection of 1.85 MBq (50 microCi) of MEGATOPE are shown in Table 4.

Method of Calculation: Hine GJ, Johnston RE: Absorbed Doses from Radionuclides, J. Nucl Med 11:468-469,1970.

HOW SUPPLIED

MEGATOPE (iodinated I 131 albumin) injection is a colorless to very pale yellow solution available in multiple-dose vials containing the following amounts of radioactivity on the date of calibration:

Complete radioassay data for each vial are provided on the MEGATOPE vial label.

STORAGE AND HANDLING

Store refrigerated at 2º to 8ºC (36° to 46°F) in suitable lead shield.

This radiopharmaceutical is licensed for distribution to facilities and persons licensed by the U.S. Nuclear Regulatory Commission or under an equivalent license issued by an Agreement State.

Iso-Tex Diagnostics, Inc. • U.S. License No. 2189
1511 Country Road 129 Alvin, TX 77511, U.S.A
(281) 482-1231 • FAX: (281) 482-1070

Revised 7/2023
Code 95-1731/Rev.002